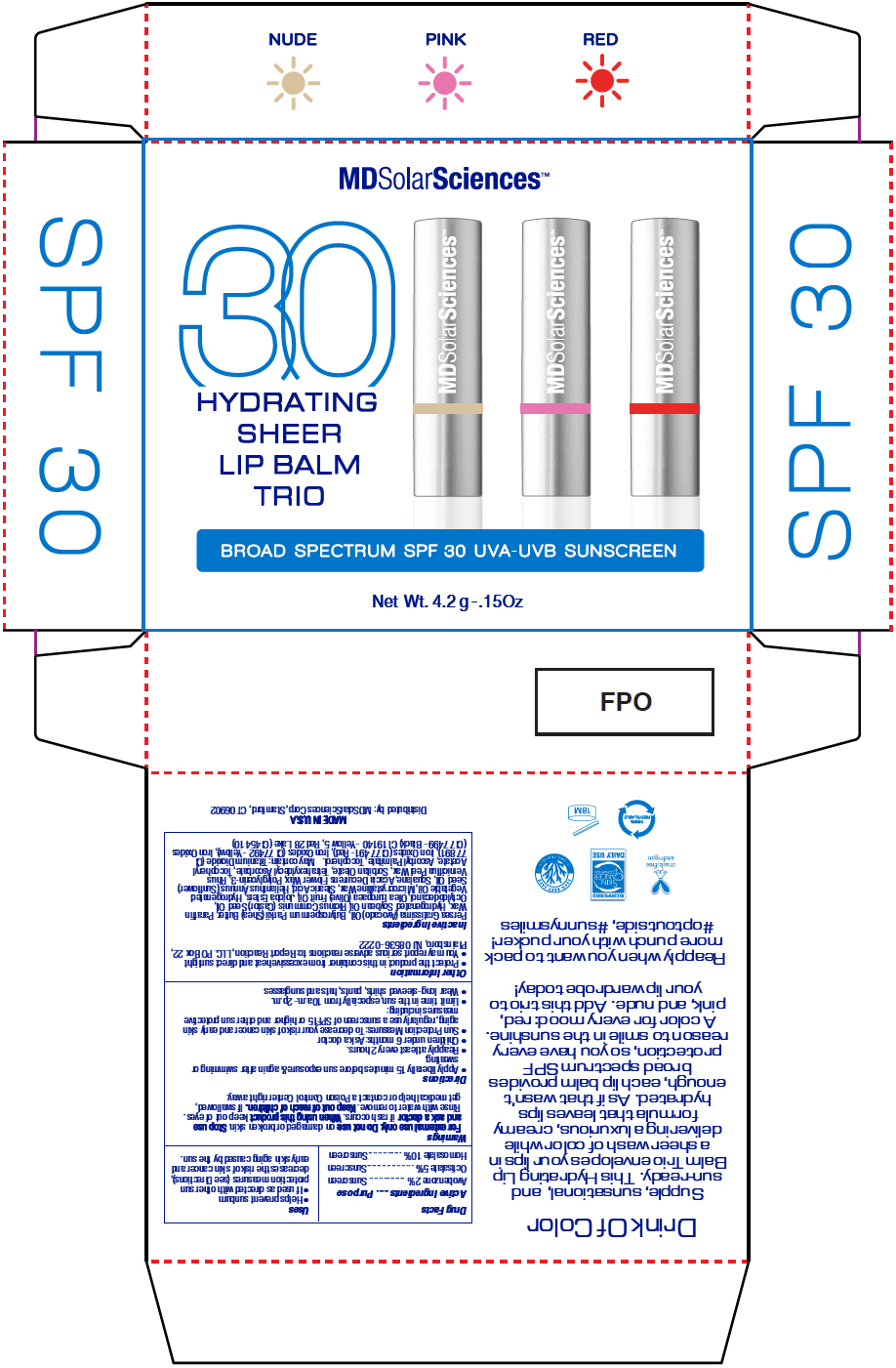 DRUG LABEL: Hydrating Sheer Lip Balm SPF 30 - TRIO
NDC: 49358-567 | Form: KIT | Route: TOPICAL
Manufacturer: MDSolarSciences
Category: otc | Type: HUMAN OTC DRUG LABEL
Date: 20190806

ACTIVE INGREDIENTS: Avobenzone 30 mg/1 g; Octisalate 50 mg/1 g; Homosalate 100 mg/1 g; Avobenzone 30 mg/1 g; Octisalate 50 mg/1 g; Homosalate 100 mg/1 g; Avobenzone 30 mg/1 g; Octisalate 50 mg/1 g; Homosalate 100 mg/1 g
INACTIVE INGREDIENTS: Avocado Oil; Shea Butter; PARAFFIN; HYDROGENATED SOYBEAN OIL; Castor Oil; OCTYLDODECANOL; OLIVE OIL; HYDROGENATED JOJOBA OIL, RANDOMIZED; CORN OIL; MICROCRYSTALLINE WAX; STEARIC ACID; SUNFLOWER OIL; SQUALANE; ACACIA DECURRENS FLOWER WAX; POLYGLYCERIN-3; TOXICODENDRON VERNICIFLUUM FRUIT RIND WAX; SORBITAN MONOOLEATE; TETRAHEXYLDECYL ASCORBATE; .ALPHA.-TOCOPHEROL ACETATE; ASCORBYL PALMITATE; TOCOPHEROL; TITANIUM DIOXIDE; FERRIC OXIDE RED; FERRIC OXIDE YELLOW; FERROSOFERRIC OXIDE; FD&C YELLOW NO. 5; D&C RED NO. 28; Avocado Oil; Shea Butter; PARAFFIN; HYDROGENATED SOYBEAN OIL; Castor Oil; OCTYLDODECANOL; OLIVE OIL; HYDROGENATED JOJOBA OIL, RANDOMIZED; CORN OIL; MICROCRYSTALLINE WAX; STEARIC ACID; SUNFLOWER OIL; SQUALANE; ACACIA DECURRENS FLOWER WAX; POLYGLYCERIN-3; TOXICODENDRON VERNICIFLUUM FRUIT RIND WAX; SORBITAN MONOOLEATE; TETRAHEXYLDECYL ASCORBATE; .ALPHA.-TOCOPHEROL ACETATE; ASCORBYL PALMITATE; TOCOPHEROL; TITANIUM DIOXIDE; FERRIC OXIDE RED; FERRIC OXIDE YELLOW; FERROSOFERRIC OXIDE; FD&C YELLOW NO. 5; D&C RED NO. 28; Avocado Oil; Shea Butter; PARAFFIN; HYDROGENATED SOYBEAN OIL; Castor Oil; OCTYLDODECANOL; OLIVE OIL; HYDROGENATED JOJOBA OIL, RANDOMIZED; CORN OIL; MICROCRYSTALLINE WAX; STEARIC ACID; SUNFLOWER OIL; SQUALANE; ACACIA DECURRENS FLOWER WAX; POLYGLYCERIN-3; TOXICODENDRON VERNICIFLUUM FRUIT RIND WAX; SORBITAN MONOOLEATE; TETRAHEXYLDECYL ASCORBATE; .ALPHA.-TOCOPHEROL ACETATE; ASCORBYL PALMITATE; TOCOPHEROL; TITANIUM DIOXIDE; FERRIC OXIDE RED; FERRIC OXIDE YELLOW; FERROSOFERRIC OXIDE; FD&C YELLOW NO. 5; D&C RED NO. 28

Hydrating Sheer Lip Balm SPF 30 - TRIO

Drug Facts

ACTIVE INGREDIENT

Active Ingredients | Purpose
Avobenzone 2% | Sunscreen
Octisalate 5% | Sunscreen
Homosalate 10% | Sunscreen

Uses

- Helps prevent sunburn
- If used as directed with other sun protection measures (see Directions), decreases the risk of skin cancer and early skin aging caused by the sun.

Warnings

For external use only. Do not use on damaged or broken skin. Stop use and ask a doctor if rash occurs. When using this product keep out of eyes. Rinse with water to remove.

Keep out of reach of children. If swallowed, get medical help or contact a Poison Control Center right away.

Directions

- Apply liberally 15 minutes before sun exposure & again after swimming or sweating.
- Reapply at least every 2 hours.
- Children under 6 months: Ask a doctor
- Sun Protection Measures: To decrease your risk of skin cancer and early skin aging, regularly use a sunscreen of SPF15 or higher and other sun protective measures including:
- Limit time in the sun, especially from 10a.m.-2p.m.
- Wear long-sleeved shirts, pants, hats and sunglasses

Other Information

- Protect the product in this container from excessive heat and direct sunlight
- You may report serious adverse reactions to: Report Reaction, LLC. PO Box 22, Plainsboro, NJ 08536-0222

Inactive Ingredients

Persea Gratissima (Avocado) Oil, Butyrospermum Parkii (Shea) Butter, Paraffin Wax, Hydrogenated Soybean Oil, Ricinus Communis (Castor) Seed Oil, Octyldodecanol, Olea Europaea (Olive) Fruit Oil, Jojoba Esters, Hydrogenated Vegetable Oil, Microcrystalline Wax, Stearic Acid, Helianthus Annuus (Sunflower) Seed Oil, Squalane, Acacia Decurrens Flower Wax, Polyglycerin-3, Rhus Verniciflua Peel Wax, Sorbitan Oleate, Tetrahexyldecyl Ascorbate, Tocopheryl Acetate, Ascorbyl Palmitate, Tocopherol. May contain: Titanium Dioxide (CI 77891), Iron Oxides (CI 77491- Red), Iron Oxides (CI 77492 - Yellow), Iron Oxides (CI 77499 - Black) CI 19140 - Yellow 5, Red 28 Lake (CI 45410)

Distributed by: MDSolarSciences Corp, Stamford, CT 06902

PRINCIPAL DISPLAY PANEL - Kit Carton

MDSolarSciences™

30
HYDRATING
SHEER
LIP BALM
TRIO

BROAD SP ECTRUM SPF 30 UVA- UVB SUNSCRE EN

Net Wt. 4.2 g -.15Oz